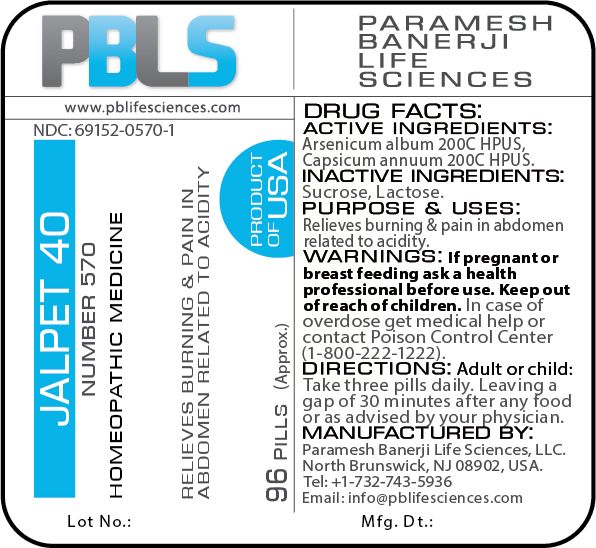 DRUG LABEL: Jalpet 40 (Number 570)
NDC: 69152-0570 | Form: PELLET
Manufacturer: Paramesh Banerji Life Sciences LLC
Category: homeopathic | Type: HUMAN OTC DRUG LABEL
Date: 20180702

ACTIVE INGREDIENTS: CAPSICUM 200 [hp_C]/1 1; ARSENIC TRIOXIDE 200 [hp_C]/1 1
INACTIVE INGREDIENTS: LACTOSE; SUCROSE

DRUG FACTS: Active Ingredients

Arsenicum album 200C HPUS, Capsicum annuum 200C HPUS

Inactive Ingredients

Sucrose, Lactose

Purpose

Relieves burning & pain in abdomen related to acidity

Uses

Relieves burning & pain in abdomen related to acidity

Warnings

If pregnant or breast feeding ask a health professional before use.

Keep out of reach of children. In case of overdose, get medical help or contact a Poison Control Center (1-800-222-1222) right away.

Direction

Adult or child: Take three pills daily. Leaving a gap of 30 minutes after any food or as advised by your physician.

Manufactured by

Paramesh Banerji Life Sciences, LLC.

North Brunswick, NJ 08902, USA.

Tel: +1-732-743-5936

Email: info@pblifesciences.com

Principal Display Panel

NDC: 69152-0570-1

Jalpet 40

Number 570

Homeopathic Medicine

Relieves burning & pain in abdomen related to acidity

96 Pills (Approx.)

Product of USA